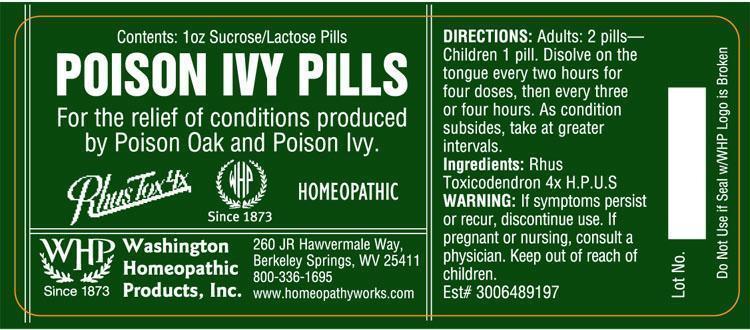 DRUG LABEL: Poison Ivy Pills
NDC: 68428-723 | Form: PELLET
Manufacturer: Washington Homeopathic Products
Category: homeopathic | Type: HUMAN OTC DRUG LABEL
Date: 20191223

ACTIVE INGREDIENTS: TOXICODENDRON PUBESCENS LEAF 4 [hp_X]/28 g
INACTIVE INGREDIENTS: SUCROSE; LACTOSE

DRUG FACTS

ACTIVE INGREDIENTS

RHUS TOX 4X

USES

To relieve the symptoms of conditions produced by Poison Oak and Poison Ivy

KEEP OUT OF REACH OF CHILDREN

Keep this and all medicines out of reach of children.

INDICATIONS

RHUS TOX Better motion

STOP USE AND ASK DOCTOR

If symptoms persist/worsen discontinue use. If pregnant/nursing, consult a physician.

DIRECTIONS

Adults 2 pellets every 2 hours for 4 doses. Then every 3 or 4 hours. As condition subsides, take at greater intervals.

Children: 1 pellet.

INACTIVE INGREDIENTS

Sucrose/Lactose

PRINCIPAL DISPLAY PANEL

Enter section text here